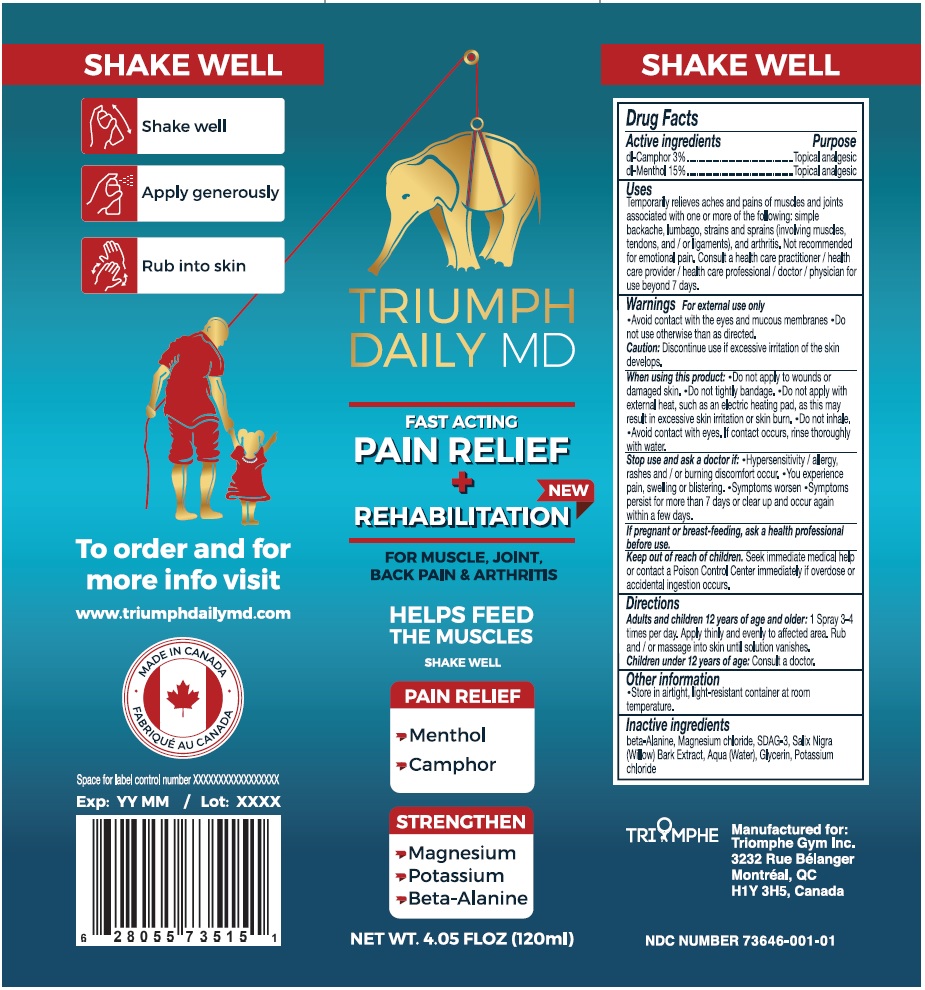 DRUG LABEL: TRIUMPH DAILY MD
NDC: 73646-001 | Form: SPRAY
Manufacturer: Dolotech inc.
Category: otc | Type: HUMAN OTC DRUG LABEL
Date: 20200217

ACTIVE INGREDIENTS: CAMPHOR (SYNTHETIC) 30 mg/1 mL; RACEMENTHOL 150 mg/1 mL
INACTIVE INGREDIENTS: WILLOW BARK; SALIX ALBA BARK; ALCOHOL; WATER; GLYCERIN; .BETA.-ALANINE; POTASSIUM CHLORIDE; MAGNESIUM CHLORIDE

Drug Facts

Active ingredients Purpose
dl-Camphor 3% ....................................... Topical analgesic
dL-Menthol 15% ......................................... Topical analgesic

Uses

Temporarily relieves aches and pains of muscles and joints associated with one or more of the following:simple backache, lumbago, strains and sprains (involving muscles, tendons and /or ligaments) and arthritis.

Not recommended for emotional pain. Consult a healthcare practitioner / health care provider / health care professional / doctor / physician for use beyond 7 days.

Warnings
For external use only
• Avoid contact with the eyes and mucous membranes. Do ont use otherwise than as directed.

Caution: Discontinue use if excessive irritation of the skin develops.

When using this product

Do not apply to wounds or damaged skin.

Do not tightly bandage.

Do not apply with external heat, such as electric heating pad, as this may result in excessive skin irritation or skin burn.

Do not inhale.

Avoid contact with eyes. If contact occurs, rinse thoroughly with water.

Stop use and ask a doctor if • Hypersensitivity / allergy, rashes and or burning discomfort occur. • You experience pain, swelling or blistering. •Symptoms worsens •Symptoms persist for more than 7 days or clear up and occur again within a few days.

If pregnant or breast-feeding, ask a health professional before use.

Keep out of reach of children.

Seek immediate medical help or contact a Poison Control Center immediately if overdose or accidental ingestion occurs.

Directions

Adults and children 12 years of age and older: 1 Spray 3-4 times per day. Apply thinly and evenly to affected area. Rub and / or massage into skin until solution vannishes.

Children under 12 years of age: Consult a doctor.

Other information

- Store in airtight, light-resistant container at room temperature.

Inactive ingredients

beta-Alanine, Magnesium chloride, SDAG-3, Salix Nigra (Willow) Bark Extract, Aqua (Water), Glycerin, Potassium chloride.